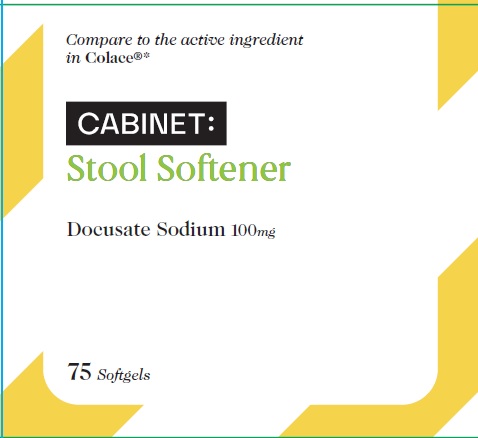 DRUG LABEL: DOCUSATE SODIUM
NDC: 68210-4104 | Form: CAPSULE, LIQUID FILLED
Manufacturer: Spirit Pharmaceuticals LLC
Category: otc | Type: HUMAN OTC DRUG LABEL
Date: 20241213

ACTIVE INGREDIENTS: DOCUSATE SODIUM 100 mg/1 1
INACTIVE INGREDIENTS: POLYETHYLENE GLYCOL 400; PROPYLENE GLYCOL; WATER; GELATIN; GLYCERIN; SORBITOL; FD&C RED NO. 40; FD&C YELLOW NO. 6; TITANIUM DIOXIDE

Docusate Sodium 100mg

Drug Facts

Active ingredient (in each softgel)

Docusate Sodium 100 mg

Purpose

Stool Softner

Uses

- for temporary relief of occasional constipation and irregularity
- this product generally produces a bowel movement within 12 to 72 hours

Warnings

Ask a doctor before use if you have

- stomach pain, nausea or vomittiong
- a sudden change in bowel habits that lasts more than 2 weeks

Stop use and ask a doctor if

- you have rectal bleeding or fail to have a bowel movement after use of a laxative. These could be signs of a serious condition.
- you need to use laxative for more than 1 week.

PREGNANCY OR BREAST FEEDING

If pregnant or breast-feeding, ask a health professional before use.

Keep out of reach of children. In case of overdose, get medical help or contact a Poison Control Center right away.1(800)222-1222

Directions

- take only by mouth. Doses may be taken as a single daily dose or in divided doses.

Adults and children 12 years and over | 1 to 3 softgels daily. This dose may be taken as a single daily dose or in divided doses
Children 2 to under 12 years of age | 1 softgel daily.
Children under 2 years of age | Ask a doctor

Other information

- Store at 25°C (77°F) excursions permitted between 15°-30°C (59°-86°F)
- Keep tightly closed

Inactive ingredients

FD&C Red#40, FD&C Yellow#6, gelatin, glycerin, polyethylene glycol 400, propylene glycol, purified water, sorbitol solution, titanium dioxide.

Questions or comments?

1-888-333-9792

PDP

Cabinet:
Stool Softener
Docusate Sodium 100mg

75 Softgels